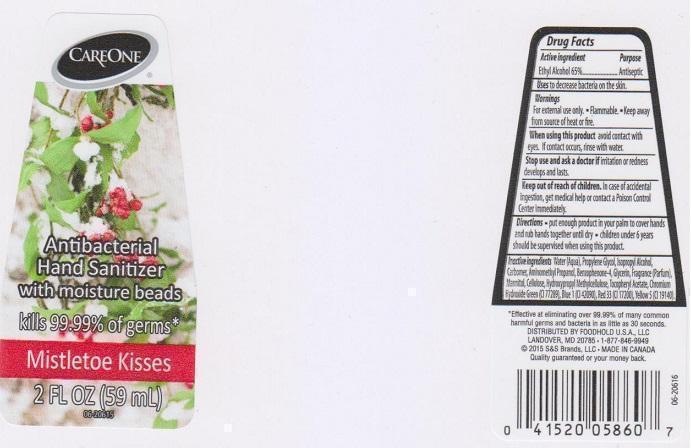 DRUG LABEL: CAREONE ANTIBACTERIAL HAND SANITIZER
NDC: 41520-417 | Form: LIQUID
Manufacturer: AMERICAN SALES COMPANY
Category: otc | Type: HUMAN OTC DRUG LABEL
Date: 20150625

ACTIVE INGREDIENTS: ALCOHOL 650 mg/1 mL
INACTIVE INGREDIENTS: WATER; PROPYLENE GLYCOL; ISOPROPYL ALCOHOL; CARBOMER 934; AMINOMETHYLPROPANOL; SULISOBENZONE; GLYCERIN; MANNITOL; POWDERED CELLULOSE; HYPROMELLOSES; .ALPHA.-TOCOPHEROL ACETATE; CHROMIUM HYDROXIDE GREEN; FD&C BLUE NO. 1; D&C RED NO. 33; FD&C YELLOW NO. 5

DRUG FACTS

ACTIVE INGREDIENT

ETHYL ALCOHOL 65%

PURPOSE

ANTISEPTIC

USES

TO DECREASE BACTERIA ON THE SKIN

WARNINGS

FOR EXTERNAL USE ONLY.

- FLAMMABLE
- KEEP AWAY FROM SOURCE OF HEAT OR FIRE

WHEN USING THIS PRODUCT

AVOID CONTACT WITH EYES. IF CONTACT OCCURS, RINSE WITH WATER

STOP USE AND ASK A DOCTOR IF

IRRITATION OR REDNESS DEVELOPS AND LASTS

KEEP OUT OF REACH OF CHILDREN

IN CASE OF ACCIDENTAL INGESTION, GET MEDICAL HELP OR CONTACT A POISON CONTROL CENTER IMMEDIATELY

DIRECTIONS

- PUT ENOUGH PRODUCT IN YOUR PALM TO COVER HANDS AND RUB HANDS TOGETHER UNTIL DRY
- CHILDREN UNDER 6 YEARS SHOULD BE SUPERVISED WHEN USING THIS PRODUCT

INACTIVE INGREDIENTS

WATER (AQUA), PROPYLENE GLYCOL, ISOPROPYL ALCOHOL, CARBOMER, AMINOMETHYL PROPANOL, BENZOPHENONE-4, GLYCERIN, FRAGRANCE (PARFUM), MANNITOL, CELLULOSE, HYDROXYPROPYL METHYLCELLULOSE, TOCOPHERYL ACETATE, CHROMIUM HYDROXIDE GREEN (CI 77289), BLUE 1 (CI 42090), RED 33 (CI 17200), YELLOW 5 (CI 19140)